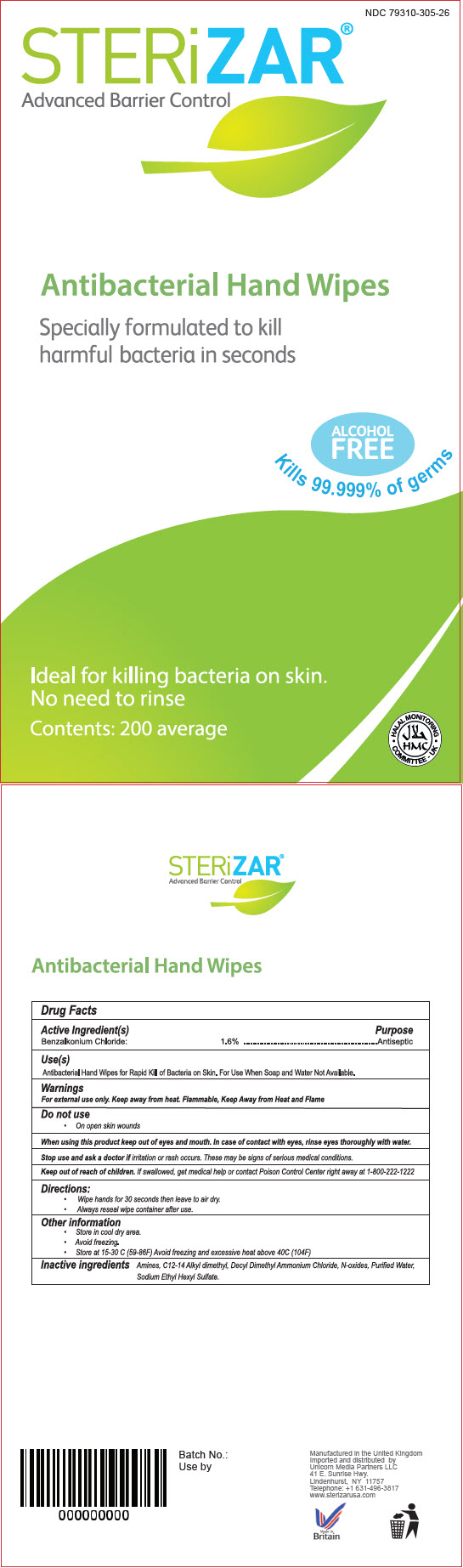 DRUG LABEL: STERiZAR 
NDC: 79310-305 | Form: CLOTH
Manufacturer: Unicorn Media Partners LLC
Category: otc | Type: HUMAN OTC DRUG LABEL
Date: 20220114

ACTIVE INGREDIENTS: Benzalkonium Chloride 16 mg/1 mL
INACTIVE INGREDIENTS: DIDECYLDIMONIUM CHLORIDE; SODIUM ETHASULFATE; WATER

STERiZAR®
Advanced Barrier Control

Drug Facts

Active Ingredient(s)

Benzalkonium Chloride 1.6 %

Purpose

Antiseptic

Use

Antibacterial Hand Wipes for Rapid Kill of Bacteria on Skin. For Use When Soap and Water Not Available.

Warnings

For external use only. Keep away from heat. Flammable, Keep Away from Heat and Flame

Do not use

- On open skin wounds

When using this product keep out of eyes and mouth. In case of contact with eyes, rinse eyes thoroughly with water.

Stop use and ask a doctor if irritation or rush occurs These may be sign of serious medical conditions.

Keep out of reach of children. If swallowed, get medical help or contact Poison Control Center right away at 1-800-222-1222

Directions

- Wipe hands for 30 seconds then leave to air dry.
- Always reseal wipe container after use.

Other information

- Store in cool dry area.
- Avoid freezing
- Store at 15-30 C (59-86F) Avoid freezing and excessive heat above 40C (104F)

Inactive ingredients

Amines, C12-14 Alkyl dimethyl, Decyl Dimethyl Ammonium Chloride, N-oxides, Purified Water, Sodium Ethyl Hexyl Sulfate.

Imported and distributed by
Unicorn Media Partners LLC
41 E. Sunrise Hwy.
Lindenhurst, NY 11757

PRINCIPAL DISPLAY PANEL - 200 Wipe Bag Label

NDC 79310-305-26

STERiZAR®
Advanced Barrier Control

Antibacterial Hand Wipes

Specially formulated to kill
harmful bacteria in seconds

ALCOHOL
FREE

Kills 99.999% of germs

Ideal for killing bacteria on skin.
No need to rinse

Contents: 200 average

• HALAL MONITORING •
COMMITTEE - UK